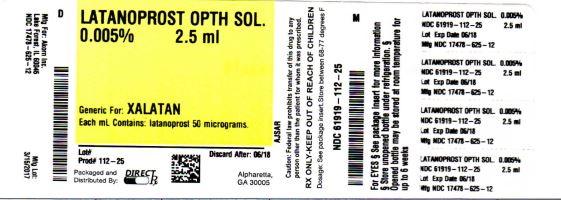 DRUG LABEL: LATANOPROST
NDC: 61919-112 | Form: SOLUTION/ DROPS
Manufacturer: DIRECT RX
Category: prescription | Type: HUMAN PRESCRIPTION DRUG LABEL
Date: 20200120

ACTIVE INGREDIENTS: LATANOPROST 50 ug/1 mL
INACTIVE INGREDIENTS: BENZALKONIUM CHLORIDE; SODIUM PHOSPHATE, MONOBASIC; WATER; SODIUM CHLORIDE; SODIUM PHOSPHATE, DIBASIC, ANHYDROUS

LATANOPROST

Rx only
Sterile

DESCRIPTION

Latanoprost is a prostaglandin F2α analogue. Its chemical name is isopropyl-(Z)-7 [(1R,2R,3R,5S) 3,5-dihydroxy-2-[(3R)-3-hydroxy-5-phenylpentyl]cyclopentyl]-5-heptenoatft Its molecular formula is C26H4O5 and its chemical structure is:

[Chemical Structure]

Latanoprost is a colorless to slightly yellow oil that is very soluble in acetonitrile and freely soluble in acetone, ethanol, ethyl acetate, Isopropanol, methanol and octanol. It Is practically Insoluble In water.

Latanoprost Ophthalmic Solution, 0.005% is supplied as a sterile, isotonic, buffered aqueous solution of latanoprost with a pH of approximately 6.7 and an osmolality of approximately 267 mOsmol/kg. Each mL of Latanoprost Ophthalmic Solution, 0.005% contains 50 micrograms of latanoprost Benzalkonium chloride, 0.02% is added as a preservative. The inactive ingredients are: sodium chloride, sodium dihydrogen phosphate monohydrate, disodium hydrogen phosphate anhydrous and water for injection. One drop contains approximately 1.5 μg of latanoprost.

CLINICAL PHARMACOLOGY

Mechanism of Action

Latanoprost is a prostanoid selective FP receptor agonist that is believed to reduce the intraocular pressure (I0P) by increasing the outflow of aqueous humor. Studies in animals and man suggest that the main mechanism of action is increased uveoscleral outflow. Elevated IOP represents a major risk factor for glaucomatous Held loss. The higher the level of IOP, the greater the likelihood of optic nerve damage and visual field loss.

Pharmacokinetics/Pharmacodynamics

Absorption: Latanoprost is absorbed through the cornea where the isopropyl ester prodrug is hydrolyzed to the acid form to become biologically active. Studies in man indicate that the peak concentration in the aqueous humor is reached about two hours after topical administration.

Distributioin: The distribution volume in humans is 0.16 ± 0.02 L/kg. The acid of latanoprost can be measured in aqueous humor during the first 4 hours, and in plasma only during the first hour after local administration.

Metabolism: Latanoprost, an Isopropyl ester prodrug, Is hydrolyzed by esterases In the cornea to the biologically active acid. The active acid of latanoprost reaching the systemic circulation is primarily metabolized by the liver to the 1,2-dinor and 1,2,3,4-tetranor metabolites via fatty acid β-oxidation.

Excretion: The elimination of the acid of latanoprost from human plasma is rapid (t1/2 = 17 min) after both intravenous and topical administration. Systemic clearance Is approximately 7 mL/min/kg. Following hepatic β-oxidatlon, the metabolites are mainly eliminated via the kidneys. Approximately 88% and 98% of the administered dose is recovered in the urine after topical and intravenous dosing, respectively.

Animal Studies

In monkeys, latanoprost has been shown to induce increased pigmentation of the iris. The mechanism of increased pigmentation seems to be stimulation of melanin production In melanocytes of the Iris, with no proliferative changes observed. The change In iris color may be permanent

Ocular administration of latanoprost at a dose of 6 μg/eye/day (4 times the daily human dose) to cynomolgus monkeys has also been shown to induce increased palpebral fissure. This effect was reversible upon discontinuation of the drug.

INDICATIONS AND USAGE

Latanoprost Ophthalmic Solution, 0.005% is indicated for the reduction of elevated intraocular pressure in patients with open- angle glaucoma or ocular hypertension.

CLINICAL STUDIES

Patients with mean baseline intraocular pressure of 24 - 25 mmHg who were treated for 6 months in multi-center, randomized, controlled trials demonstrated 6-8 mmHg reductions in intraocular pressure. This IOP reduction with Latanoprost Ophthalmic Solution, 0.005% dosed once daily was equivalent to the effect of timolol 0.5% dosed twice daily.

A 3-year open-label, prospective safety study with a 2-year extension phase was conducted to evaluate the progression of increased iris pigmentation with continuous use of Latanoprost Ophthalmic Solution, 0.005% once-daily as adjunctive therapy In 519 patients with open-angle glaucoma. The analysis was based on observed-cases population of the 380 patients who continued in the extension phase.

Results showed that the onset of noticeable increased iris pigmentation occurred within the first year of treatment for the majority of the patients who developed noticeable increased iris pigmentation. Patients continued to show signs of increasing Iris pigmentation throughout the five years of the study. Observation of Increased Iris pigmentation did not affect the Incidence, nature or severity of adverse events (other than increased iris pigmentation) recorded in the study. IOP reduction was similar regardless of the development of increased iris pigmentation during the study.

CONTRAINDICATIONS

Known hypersensitivity to latanoprost, benzalkonium chloride or any other ingredients in this product.

WARNINGS

Latanoprost Ophthalmic Solution, 0.005% has been reported to cause changes to pigmented tissues. The most frequently reported changes have been increased pigmentation of the iris, periorbital tissue (eyelid) and eyelashes, and growth of eyelashes. Pigmentation is expected to increase as long as Latanoprost Ophthalmic Solution, 0.005% is administered. After discontinuation of Latanoprost Ophthalmic Solution, 0.005%, pigmentation of the iris is likely to be permanent while pigmentation of the periorbital tissue and eyelash changes have been reported to be reversible In some patients. Patients who receive treatment should be informed of the possibility of increased pigmentation. The effects of increased pigmentation beyond 5 years are not known.

PRECAUTIONS

General: Latanoprost Ophthalmic Solution, 0.005% may gradually increase the pigmentation of the iris. The eye color change is due to increased melanin content in the stromal melanocytes of the iris rather than to an increase in the number of melanocytes. This change may not be noticeable for several months to years (see WARNINGS). Typically, the brown pigmentation around the pupil spreads concentrically towards the periphery of the iris and the entire iris or parts of the iris become more brownish. Neither nevi nor freckles of the iris appear to be affected by treatment. While treatment with Latanoprost Ophthalmic Solution, 0.005% can be continued in patients who develop noticeably increased iris pigmentation, these patients should be examined regularly. During clinical trials, the increase in brown iris pigment has not been shown to progress further upon discontinuation of treatment, but the resultant color change may be permanent.

Eyelid skin darkening, which may be reversible, has been reported in association with the use of Latanoprost Ophthalmic Solution, 0.005% (see WARNINGS).

Latanoprost Ophthalmic Solution, 0.005% may gradually change eyelashes and vellus hair in the treated eye; these changes include increased length, thickness, pigmentation, the number of lashes or hairs, and misdirected growth of eyelashes. Eyelash changes are usually raveisible upon discontinuation of treatment.

Latanoprost Ophthalmic Solution, 0.005% should be used with caution in patients with a history of intraocular inflammation (iritis/ uveitis) and should generally not be used in patients with active intraocular inflammation.

Macular edema, including cystoid macular edema, has been reported during treatment with Latanoprost Ophthalmic Solution, 0.005%. These reports have mainly occurred in aphakic patients, in pseudophakic patients with a torn posterior lens capsule, or in patients with known risk factors for macular edema. Latanoprost Ophthalmic Solution, 0.005% should be used with caution in patients who do not have an intact posterior capsule or who have known risk factors for macular edema.

There is limited experience with Latanoprost Ophthalmic Solution, 0.005% in the treatment of angle closure, inflammatory or neovascular glaucoma.

There have been reports of bacterial keratitis associated with the use of multiple-dose containers of topical ophthalmic products. These containers had been inadvertently contaminated by patients who, in most cases, had a concurrent corneal disease or a disruption of the ocular epithelial surface (see PRECAUTIONS, INFORMATION FOR PATIENTS).

Contact lenses should be removed prior to the administration of Latanoprost Ophthalmic Solution, 0.005%, and may be reinserted 15 minutes after administration (see PRECAUTIONS, INFORMATION FOR PATIENTS).

Information for Patients (see WARNINGS and PRECAUTIONS): Patients should be advised about the potential for increased brown pigmentation of the iris, which may be permanent. Patients should also be informed about the possibility of eyelid skin darkening, which may be reversible after discontinuation of Latanoprost Ophthalmic Solution, 0.005%.

Patients should also be Informed of the possibility of eyelash and veilus hair changes in the treated eye during treatment with Latanoprost Ophthalmic Solution, 0.005%. These changes may result in a disparity between eyes in length, thickness, pigmentation, number of eyelashes or vellus hairs, and/or direction of eyelash growth. Eyelash changes are usually reversible upon discontinuation of treatment

Patients should be instructed to avoid allowing the tip of the dispensing container to contact the eye or surrounding structures because this could cause the tip to become contaminated by common bacteria known to cause ocular infections. Serious damage to the eye and subsequent loss of vision may result from using contaminated solutions.

Patients also should be advised that if they develop an intercurrent ocular condition (e.g., trauma, or infection) or have ocular surgery, they should immediately seek their physician's advice concerning the continued use of the multiple-dose container. Patients should be advised that If they develop any ocular reactions, particularly conjunctivitis and lid reactions, they should immediately seek their physician's advice.

Patients should also be advised that Latanoprost Ophthalmic Solution, 0.005% contains benzalkonium chloride, which may be absorbed by contact lenses. Contact lenses should be removed prior to administration of the solution. Lenses may be reinserted 15 minutes following administration of Latanoprost Ophthalmic Solution, 0.005%.

If more than one topical ophthalmic drug is being used, the drugs should be administered at least five (5) minutes apart. Drvg Interactions: In vitro studies have shown that precipitation occurs when eye drops containing thimerosal are mixed with Latanoprost Ophthalmic Solution, 0.005%. If such drugs are used they should be administered at least five (5) minutes apart.

Carcinogenesis, mutagenesis, Impairment of Fertility: Latanoprost was not mutagenic in bacteria, in mouse lymphoma or in mouse micronucleus tests.

Chromosome aberrations were observed in vitro with human lymphocytes.

Latanoprost was not carcinogenic in either mice or rats when administered by oral gavage at doses of up to 170 tig/kg/day (approximately 2,800 times the recommended maximum human dose) for up to 20 and 24 months, respectively.

Additional in vitro and in vivo studies on unscheduled DNA synthesis in rats were negative. Latanoprost has not been found to have any effect on male or female fertility in animal studies.

Pregnancy: Teratogenic Effects: Pregnancy Category C.

Reproduction studies have been performed in rats and rabbits. In rabbits an incidence of 4 of 16 dams had no viable fetuses at a dose that was approximately 80 times the maximum human dose, and the highest nonembryocidal dose in rabbits was approximately 15 times the maximum human dose. There are no adequate and well-controlled studies in pregnant women. Latanoprost Ophthalmic Solution, 0.005% should be used during pregnancy only if the potential benefit justifies the potential risk to the fetus.

Nursing Mothers: It Is not known whether this drug or Its metabolites are excreted In human milk. Because many drugs are excreted in human milk, caution should be exercised when Latanoprost Ophthalmic Solution, 0.005% is administered to a nursing woman.

Pediatric Use: Safety and effectiveness in pediatric patients have not been established.

Geriatric Use: No overall differences in safety or effectiveness have been observed between elderly and younger patients.

ADVERSE REACTIONS

Adverse events referred to In other sections of this insert:

Eyelash changes (increased length, thickness, pigmentation, and number of lashes); eyelid skin darkening; intraocular inflammation (iritis/uveitis); iris pigmentation changes; and macular edema, including cystoid macular edema (see WARNINGS and PRECAUTIONS).

Controlled Clinical Trials:

The ocular adverse events and ocular signs and symptoms reported In 5 to 15% of the patients on Latanoprost Ophthalmic Solution, 0.005% in the three 6-month, multi-center, double-masked, active-controlled trials were blurred vision, burning and stinging, conjunctival hyperemia, foreign body sensation, itching, increased pigmentation of the iris, and punctuate epithelial keratopathy.

Local conjunctival hyperemia was observed; however, less than 1 % of the patients treated with Latanoprost Ophthalmic Solution, 0.005% required discontinuation of therapy because of intolerance to conjunctival hyperemia.

In addition to the above listed ocular events/signs and symptoms, the following were reported in 1 to 4% of the patients: dry eye, excessive tearing, eye pain, lid crusting, lid discomfort/pain, lid edema, lid erythema, and photophobia.

The following events were reported in less than 1 % of the patients: conjunctivitis, diplopia and discharge from the eye.

During clinical studies, there were extremely rare reports of the following: retinal artery embolus, retinal detachment, and vitreous hemorrhage from diabetic retinopathy.

The most common systemic adverse events seen with Latanoprost Ophthalmic Solution, 0.005% were upper respiratory tract infection/cold/flu, which occurred at a rate of approximately 4%. Chest pain/angina pectoris, muscle/joint/back pain, and rash/ allergic skin reaction each occurred at a rate of 1 to 2%.

Clinical Practice: The following events have been Identified during postmerketlng use of Latanoprost Ophthalmic Solution, 0.005% in clinical practice. Because they are reported voluntarily from a population of unknown size, estimates of frequency cannot be made. The events, which have been chosen for inclusion due to either their seriousness, frequency of reporting, possible causal connection to Latanoprost Ophthalmic Solution, 0.005%, or a combination of these factors, include: asthma and exacerbation of asthma; corneal edema and erosions; dyspnea; eyelash and vellus hair changes (increased length, thickness, pigmentation, and number); eyelid skin darkening; herpes keratitis; intraocular inflammation (iritis/uveitis); keratitis; macular edema, including cystoid macular edema; misdirected eyelashes sometimes resulting in eye irritation; dizziness, headache, and toxic epidermal necrolysis.

OVERDOSAGE

Apart from ocular irritation and conjunctival or episcleral hyperemia, the ocular effects of latanoprost administered at high doses are not known. Intravenous administration of large doses of latanoprost in monkeys has been associated with transient bronchoconstriction; however, in 11 patients with bronchial asthma treated with latanoprost, bronchoconstriction was not induced. Intravenous infusion of up to 3 pg/kg in healthy volunteers produced mean plasma concentrations 200 times higher than during clinical treatment and no adverse reactions were observed. Intravenous dosages of 5.5 to 10 pg/kg caused abdominal pain, dizziness, fatigue, hot flushes, nausea and sweating.

If overdosage with Latanoprost Ophthalmic Solution, 0.005% occurs, treatment should be symptomatic.

DOSAGE AND ADMINISTRATION

The recommended dosage is one drop (1.5 μg) in the affected eye(s) once daily in the evening. If one dose is missed, treatment should continue with the next dose as normal.

The dosage of Latanoprost Ophthalmic Solution, 0.005% should not exceed once daily; the combined use of two or more prostaglandins, or prostaglandin analogs including Latanoprost Ophthalmic Solution, 0.005% is not recommended. It has been shown that administration of these prostaglandin drug products more than once daily may decrease the Intraocular pressure lowering effect or cause paradoxical elevations in IOP.

Reduction of the intraocular pressure starts approximately 3 to 4 hours after administration and the maximum effect is reached after 8 to 12 hours.

Latanoprost Ophthalmic Solution, 0.005% may be used concomitantly with other topical ophthalmic drug products to lower intraocular pressure. If more than one topical ophthalmic drug is being used, the drugs should be administered at least five (5) minutes apart.

HOW SUPPLIED

Latanoprost Ophthalmic Solution, 0.005% is a clear, isotonic, buffered, preserved colorless solution of latanoprost 0.005% (125 μg/2.5 mL). It is supplied as a 2.5 mL solution in a 5 mL clear low density polyethylene bottle with a clear low density polyethylene dropper tip, and a turquoise polyethylene screw cap.

NDC17478-625-12 2.5 mL fill, 0.005% (125 μg/2.5 mL)

Storage: Protect from light. Store unopened bottles) under refrigeration at 2° to 8°C (36° to 46°F). During shipment to the patient the bottle may be maintained at temperatures up to 40°C (104°F) for a period not exceeding 8 days. Once a bottle is opened for use, it may be stored at room temperature up to 25°C (77°F) for 6 weeks.

Rx only
Sterile

Manufactured for:
Akorm, Inc.
Lake Forest, IL 60045